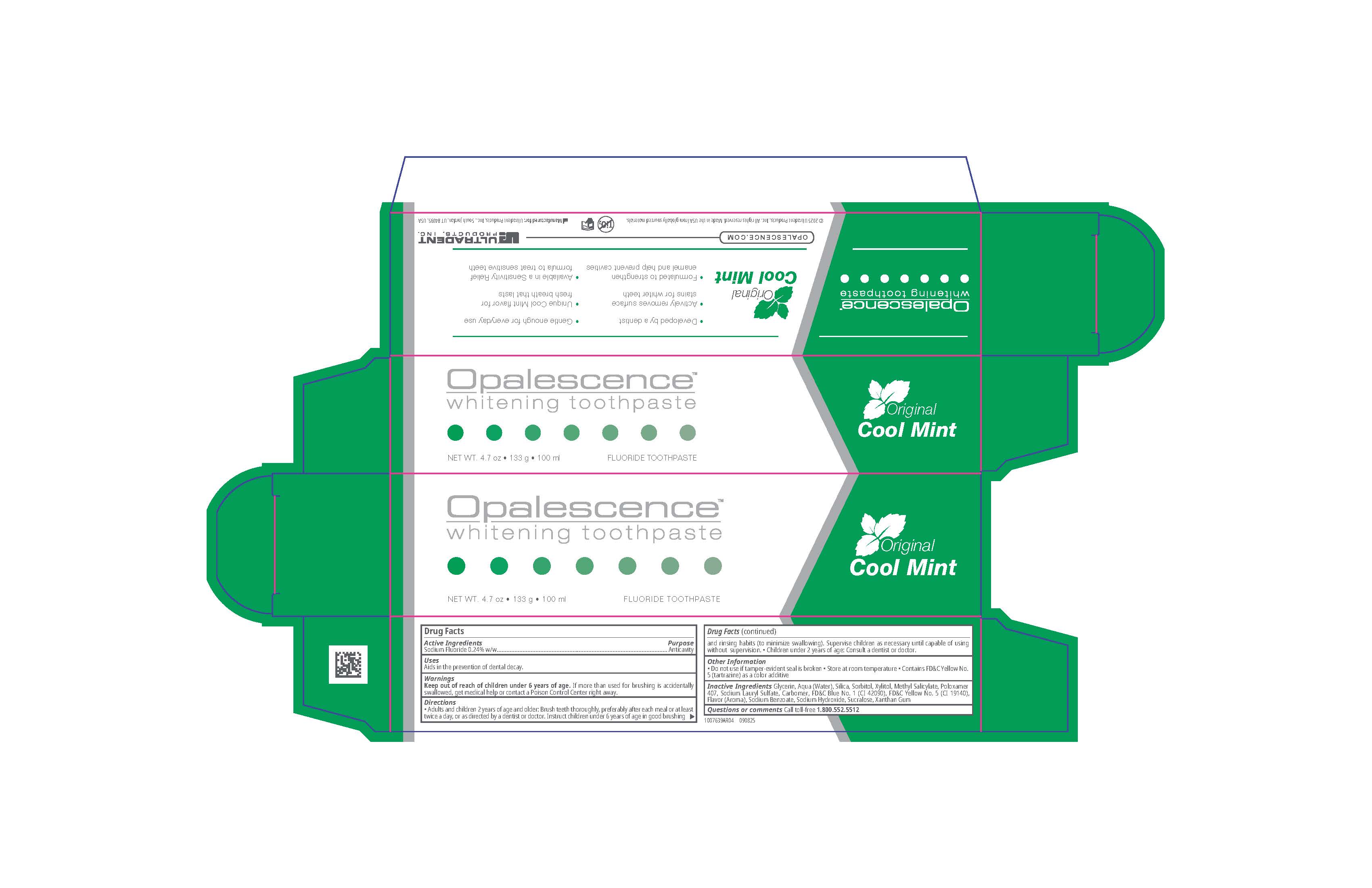 DRUG LABEL: Opalescence Whitening
NDC: 51206-314 | Form: GEL, DENTIFRICE
Manufacturer: Ultradent Products, Inc.
Category: otc | Type: HUMAN OTC DRUG LABEL
Date: 20251201

ACTIVE INGREDIENTS: SODIUM FLUORIDE 1.1 mg/1 g
INACTIVE INGREDIENTS: SODIUM LAURYL SULFATE; FD&C YELLOW NO. 5; SODIUM HYDROXIDE; AQUA; SORBITOL; SILICON DIOXIDE; POLOXAMER 407; CARBOMER; FD&C BLUE NO. 1; SODIUM BENZOATE; XYLITOL; SUCRALOSE; XANTHAN GUM; METHYL SALICYLATE; GLYCERIN

Opalescence™ Whitening Toothpaste Original Cool Mint

Drug Facts

Active Ingredients

Sodium Fluoride 0.24% w/w

Purpose

Anticavity

Uses

Aids in the prevention of dental decay

Warnings

Keep out of reach of children under 6 years of age. If more than used for brushing is accidentally swallowed, get medical help or contact a Poison Control Center right away

Directions

- Adults and children 2 years of age and older: Brush teeth thoroughly, preferably after each meal or at least twice a day, or as directed by a dentist or doctor. Instruct children under 6 years of age in good brushing and rinsing habits (to minimize swallowing). Supervise children as necessary until capable of using without supervision.
- Children under 2 years of age: Consult a dentist or doctor.

Other Information

- Do not use if tamper-evident seal is broken
- Store at room temperature
- Contains FD&C Yellow No. 5 (tartrazine) as a color additive

Inactive Ingredients

Glycerin, Aqua (Water), Silica, Sorbitol, Xylitol, Methyl Salicylate, Poloxamer 407, Sodium Lauryl Sulfate, Carbomer, FD&C Blue No. 1 (CI 42090), FD&C Yellow No. 5 (CI 19140), Flavor (Aroma), Sodium Benzoate, Sodium Hydroxide, Sucralose, Xantham Gum

Questions or Comments

Call toll-free 1.800.552.5512

PRINCIPAL DISPLAY PANEL - 4.7 oz Tube Carton

Opalescence Whitening Toothpaste

Original

Cool Mint

Fluoride Toothpaste

NET WT. 4.7 oz